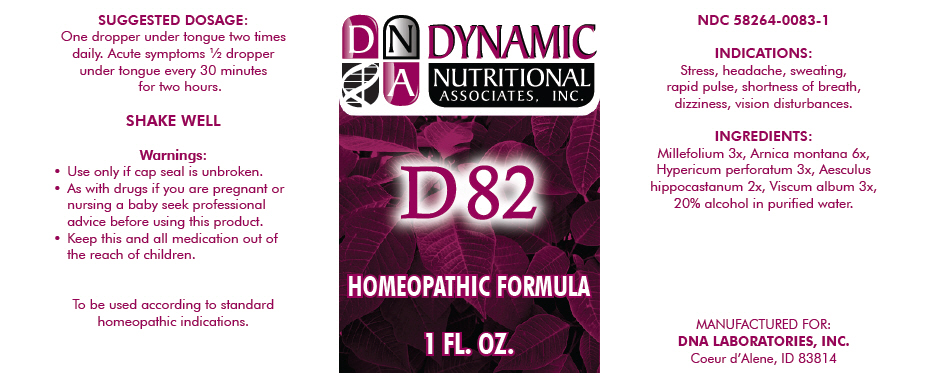 DRUG LABEL: D82
NDC: 58264-0083 | Form: SOLUTION
Manufacturer: DNA Labs, Inc.
Category: homeopathic | Type: HUMAN OTC DRUG LABEL
Date: 20250113

ACTIVE INGREDIENTS: ACHILLEA MILLEFOLIUM 3 [hp_X]/1 mL; ARNICA MONTANA 6 [hp_X]/1 mL; HYPERICUM PERFORATUM 3 [hp_X]/1 mL; HORSE CHESTNUT 2 [hp_X]/1 mL; VISCUM ALBUM WHOLE 3 [hp_X]/1 mL
INACTIVE INGREDIENTS: ALCOHOL; WATER

D82

NDC 58264-0083-1

INDICATIONS AND USAGE

INDICATIONS

Stress, headache, sweating, rapid pulse, shortness of breath, dizziness, vision disturbances.

ACTIVE INGREDIENT

INGREDIENTS

Millefolium 3x, Arnica montana 6x, Hypericum perforatum 3x, Aesculus hippocastanum 2x, Viscum album 3x, 20% alcohol in purified water.

SUGGESTED DOSAGE

One dropper under tongue two times daily. Acute symptoms ½ dropper under tongue every 30 minutes for two hours.

STORAGE AND HANDLING

SHAKE WELL

Warnings

- Use only if cap seal is unbroken.

PREGNANCY OR BREAST FEEDING

- As with drugs if you are pregnant or nursing a baby seek professional advice before using this product.

KEEP OUT OF REACH OF CHILDREN

- Keep this and all medication out of the reach of children.

To be used according to standard homeopathic indications.

PRINCIPAL DISPLAY PANEL - 1 FL. OZ. Bottle Label

DYNAMIC
NUTRITIONAL
ASSOCIATES, INC.

D 82

HOMEOPATHIC FORMULA

1 FL. OZ.